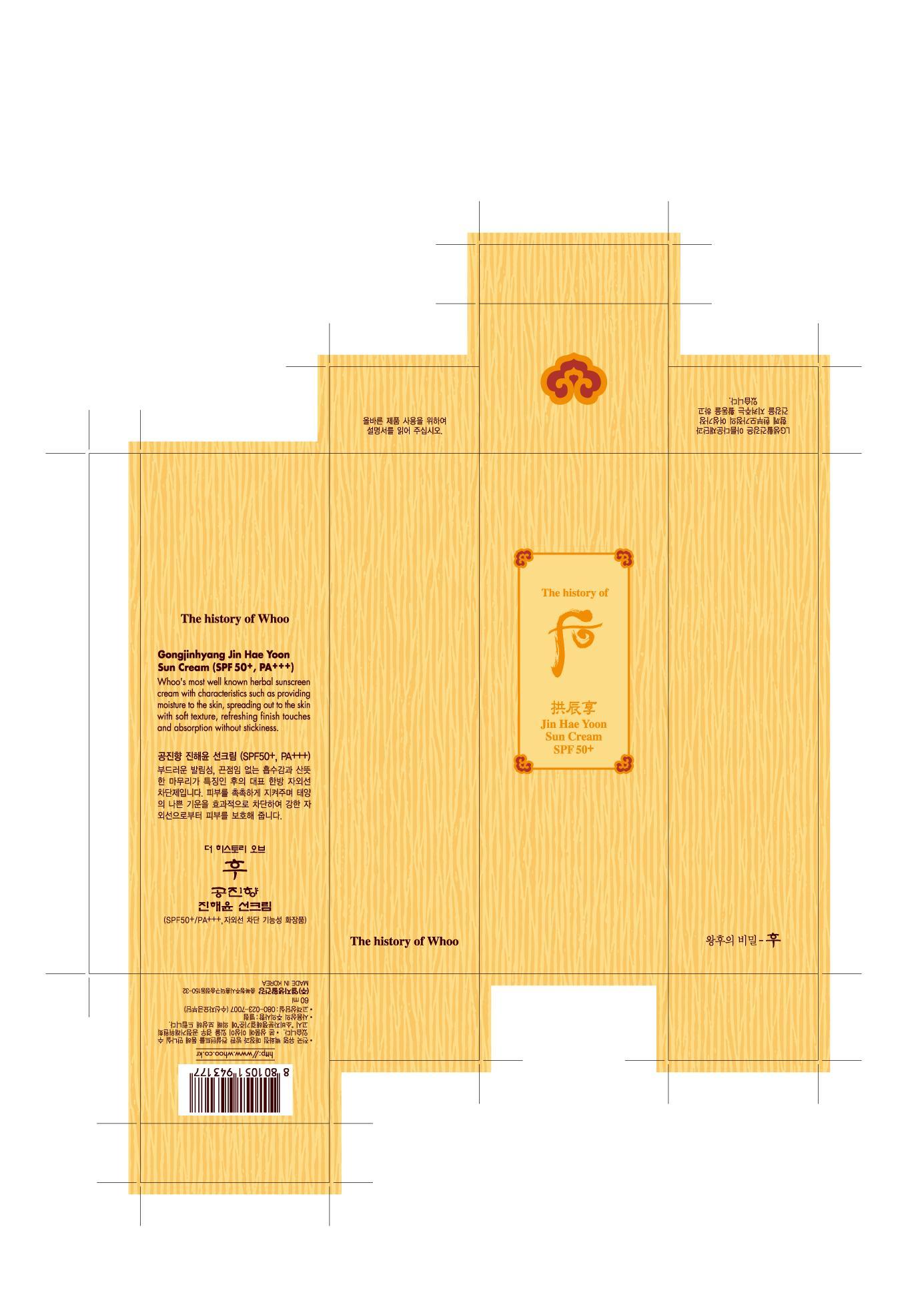 DRUG LABEL: The History of Whoo Jin Hae Yoon Sun
NDC: 53208-503 | Form: CREAM
Manufacturer: LG Household and Healthcare, Inc.
Category: otc | Type: HUMAN OTC DRUG LABEL
Date: 20110316

ACTIVE INGREDIENTS: BEMOTRIZINOL 1 mL/100 mL; OCTINOXATE 7 mL/100 mL; TITANIUM DIOXIDE 2.58 mL/100 mL; AMILOXATE 1.6 mL/100 mL; DIETHYLAMINO HYDROXYBENZOYL HEXYL BENZOATE 1 mL/100 mL
INACTIVE INGREDIENTS: WATER; TROMETHAMINE; CYCLOMETHICONE 5; DIPROPYLENE GLYCOL; CETOSTEARYL ALCOHOL; GLYCERIN; CETYL PHOSPHATE; FILIPENDULA ULMARIA ROOT; PANTHENOL; ALCOHOL; METHYLPARABEN; XANTHAN GUM; PROPYLPARABEN; ETHYLPARABEN; STEARIC ACID; EDETATE TRISODIUM; FRUIT; TROLAMINE; GLYCERYL MONOSTEARATE; AQUILARIA MALACCENSIS STEM

DRUG FACTS

WARNINGS

For external use only

Keep out of reach of children. Is swallowed, get medical help or contact a Poison Control Center right away.

WHEN USING

Keep out of eyes. Rinse with water to remove.

Stop use if a rash or irritation develops and lasts.

PACKAGE LABEL

The History of Whoo Jin Hae Yoon Sun Cream